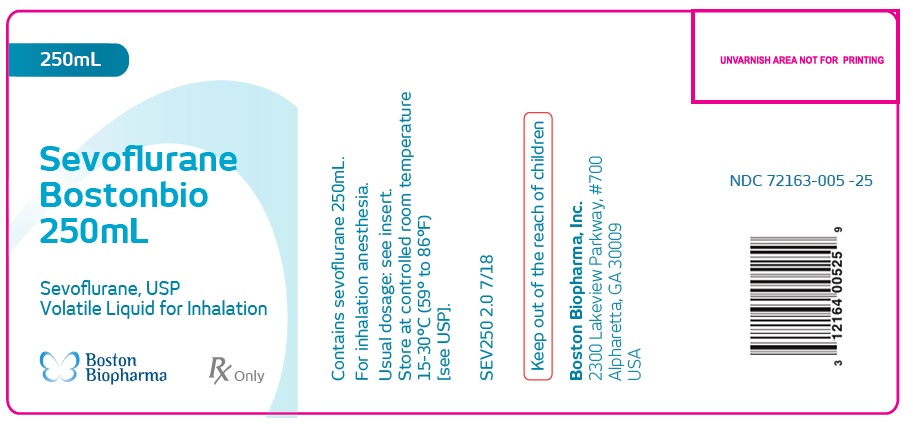 DRUG LABEL: Sevoflurane Bostonbio
NDC: 72163-005 | Form: INHALANT
Manufacturer: Boston Biopharma
Category: prescription | Type: HUMAN PRESCRIPTION DRUG LABEL
Date: 20200909

ACTIVE INGREDIENTS: SEVOFLURANE 1 mL/1 mL

HOW SUPPLIED

Sevoflurane
Bostonbio
250mL
Sevoflurane, USP
Volatile Liquid for Inhalation

Contains sevoflurane 250mL.
For inhalation anesthesia.
Usual dosage: see insert.
Store at controlled room temperature
15-30°C (59° to 86°F)
[see USP].
SEV250 2.0 7/18

Keep out of the reach of children

Boston Biopharma, Inc.
2300 Lakeview Parkway, #700
Alpharetta, GA 30009
USA

NDC 72163-005 -25

PACKAGE LABEL.PRINCIPAL DISPLAY PANEL

Sevoflurane

Bostonbio

250mL

Sevoflurane, USP

Volatile Liquid for Inhalation